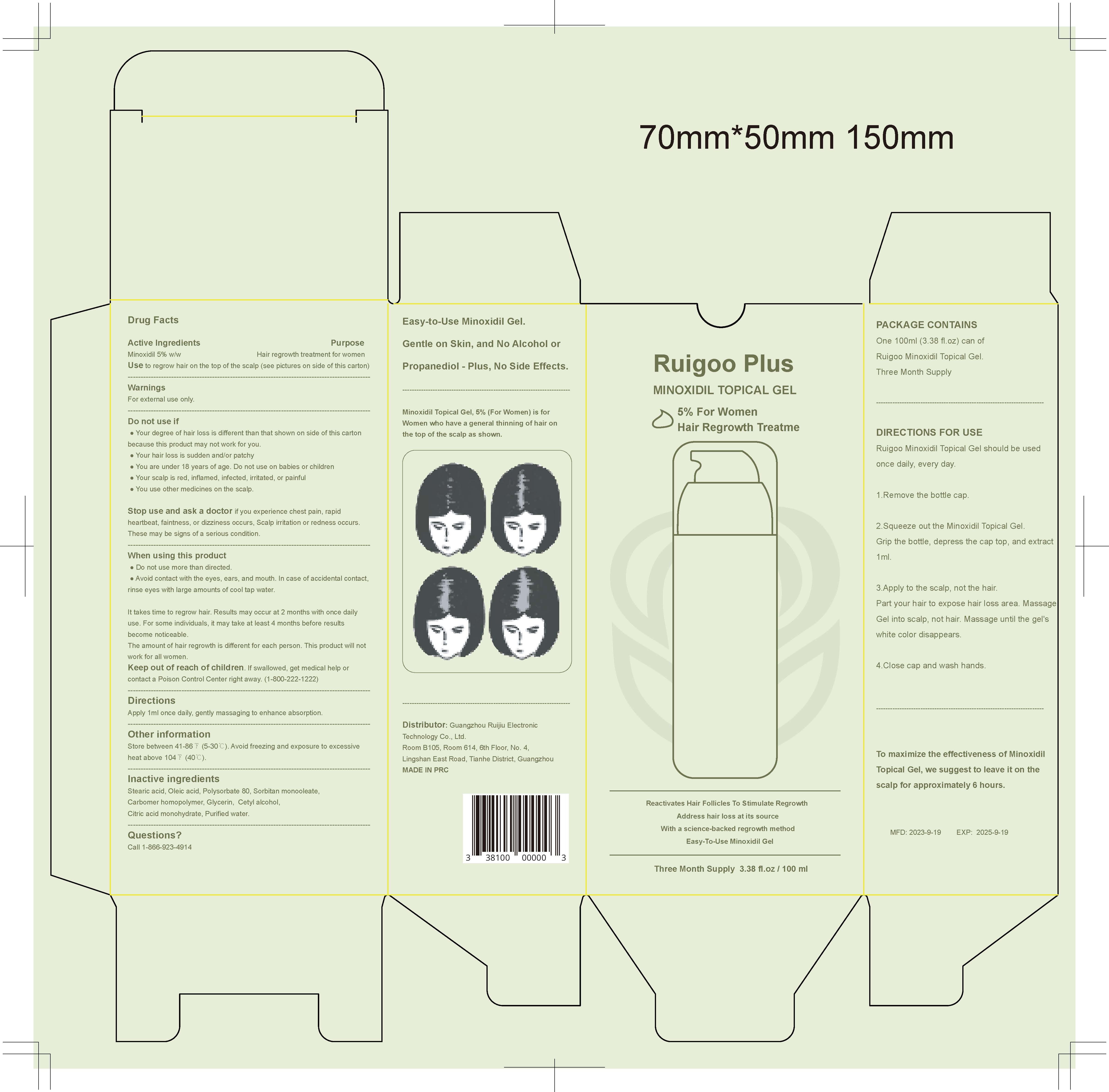 DRUG LABEL: Ruigoo Minoxidil Topical Gel
NDC: 83767-101 | Form: GEL
Manufacturer: Guangzhou Ruijiu Electronic Technology Co., Ltd.
Category: otc | Type: HUMAN OTC DRUG LABEL
Date: 20240409

ACTIVE INGREDIENTS: MINOXIDIL 5 g/100 mL
INACTIVE INGREDIENTS: CETYL ALCOHOL; GLYCERIN; POLYSORBATE 80; STEARIC ACID; SORBITAN MONOOLEATE; OLEIC ACID; CITRIC ACID MONOHYDRATE; CARBOMER HOMOPOLYMER, UNSPECIFIED TYPE; WATER

RUIGOO MINOXIDIL TOPICAL GEL

RUIGOO MINOXIDIL TOPICAL GEL

ACTIVE INGREDIENT

MINOXIDIL 5%

PURPOSE

Hair regrowth treatment for women.

Use to regrow hair on the top of the scalp.

INDICATIONS AND USAGE

is for Women who have a general thinning of hair onthe top of the scalp as shown.

WARNINGS

For external use only.

DO NOT USE

Your degree of hair loss is different than that shown on side of this cartonbecause this product may not work for you.
Your hair loss is sudden and/or patchy
You are under 18 years of age. Do not use on babies or children
Your scalp is red, inflamed, infected, irritated, or painful
You use other medicines on the scalp

Do not use more than directed.
Avoid contact with the eyes, ears, and mouth. In case of accidental contact, rinse eyes with large amounts of cool tap water.
lt takes time to regrow hair. Results may occur at 2 months with once dailyuse. For some individuals, it may take at least 4 months before resultsbecome noticeable.
The amount of hair regrowth is different for each person. This product will not work for all women.

Stop use and ask a doctor if you experience chest pain, rapidheartbeat, faintness, or dizziness occurs, Scalp irritation or redness occurs.These may be signs of a serious condition.

Keep out of reach of children. lf swallowed, get medical help orcontact a Poison Control Center right away.(1-800-222-1222)

DOSAGE AND ADMINISTRATION

Apply 1ml once daily, gently massaging to enhance absorption.

STORAGE AND HANDLING

Store between 41-86 ℉ (5-30 ℃). Avoid freezing and exposure to excessiveheat above 104 ℉ (40 ℃)

INACTIVE INGREDIENT

STEARIC ACID
OLEIC ACID
POLYSORBATE 80
SORBITAN MONOOLEATE
CARBOMER HOMOPOLYMER
CETYL ALCOHOL
CITRIC ACID MONOHYDRATE
GLYCERIN
PURIFIED WATER